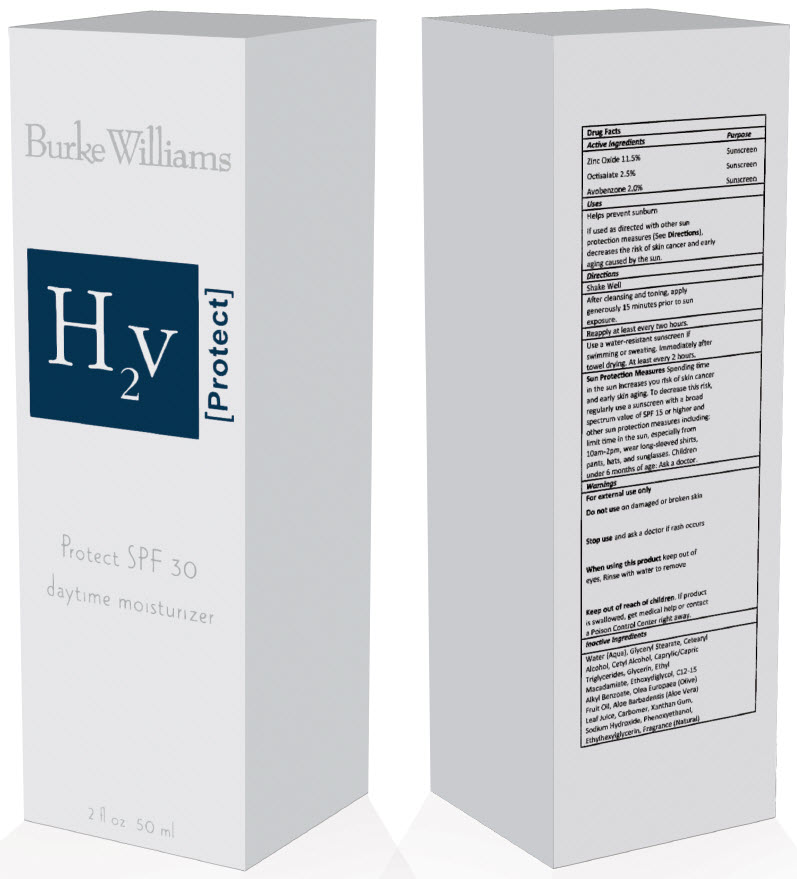 DRUG LABEL: Protect SPF 30
NDC: 70693-231 | Form: LOTION
Manufacturer: Hunter Vaughan, LLC
Category: otc | Type: HUMAN OTC DRUG LABEL
Date: 20230901

ACTIVE INGREDIENTS: ZINC OXIDE 20 mg/1 mL; OCTISALATE 3 mg/1 mL; AVOBENZONE 2 mg/1 mL
INACTIVE INGREDIENTS: WATER; GLYCERYL STEARATE SE; CETOSTEARYL ALCOHOL; CETYL ALCOHOL; MEDIUM-CHAIN TRIGLYCERIDES; GLYCERIN; ETHYL MACADAMIATE; DIETHYLENE GLYCOL MONOETHYL ETHER; ALKYL (C12-15) BENZOATE; OLIVE OIL; ALOE VERA LEAF; CARBOMER HOMOPOLYMER, UNSPECIFIED TYPE; XANTHAN GUM; SODIUM HYDROXIDE; PHENOXYETHANOL; ETHYLHEXYLGLYCERIN; FRAGRANCE 13576

Protect SPF 30

Drug Facts

ACTIVE INGREDIENT

Active Ingredients | Purpose
Zinc Oxide 11.5% | Sunscreen
Octisalate 2.5% | Sunscreen
Avobenzone 2.0% | Sunscreen

Uses

Helps prevent sunburn

If used as directed with other sun protection measures (See Directions), decreases the risk of skin cancer and early aging caused by the sun.

Directions

Shake Well

After cleansing and toning, apply generously 15 minutes prior to sun exposure.

Reapply at least every two hours.

Use a water-resistant sunscreen if swimming or sweating. Immediately after towel drying. At least every 2 hours.

Sun Protection Measures

Spending time in the sun increases you risk of skin cancer and early skin aging. To decrease this risk, regularly use a sunscreen with a broad spectrum value of SPF 15 or higher and other sun protection measures including: limit time in the sun, especially from 10am-2pm, wear long-sleeved shirts, pants, hats, and sunglasses. Children under 6 months of age: Ask a doctor.

Warnings

For external use only

Do not use on damaged or broken skin

Stop use and ask a doctor if rash occurs

When using this product keep out of eyes, Rinse with water to remove

Keep out of reach of children. If product is swallowed, get medical help or contact a Poison Control Center right away.

Inactive Ingredients

Water (Aqua), Glyceryl Stearate, Cetearyl Alcohol, Cetyl Alcohol, Caprylic/Capric Triglycerides, Glycerin, Ethyl Macadamiate, Ethoxydiglycol, C12-15 Alkyl Benzoate, Olea Europaea (Olive) Fruit Oil, Aloe Barbadensis (Aloe Vera) Leaf Juice, Carbomer, Xanthan Gum, Sodium Hydroxide, Phenoxyethanol, Ethylhexylglycerin, Fragrance (Natural)

PRINCIPAL DISPLAY PANEL - 50 ml Bottle Carton

Burke Williams

H2v
[Protect]

Protect SPF 30

daytime moisturizer

2 fl oz 50 ml